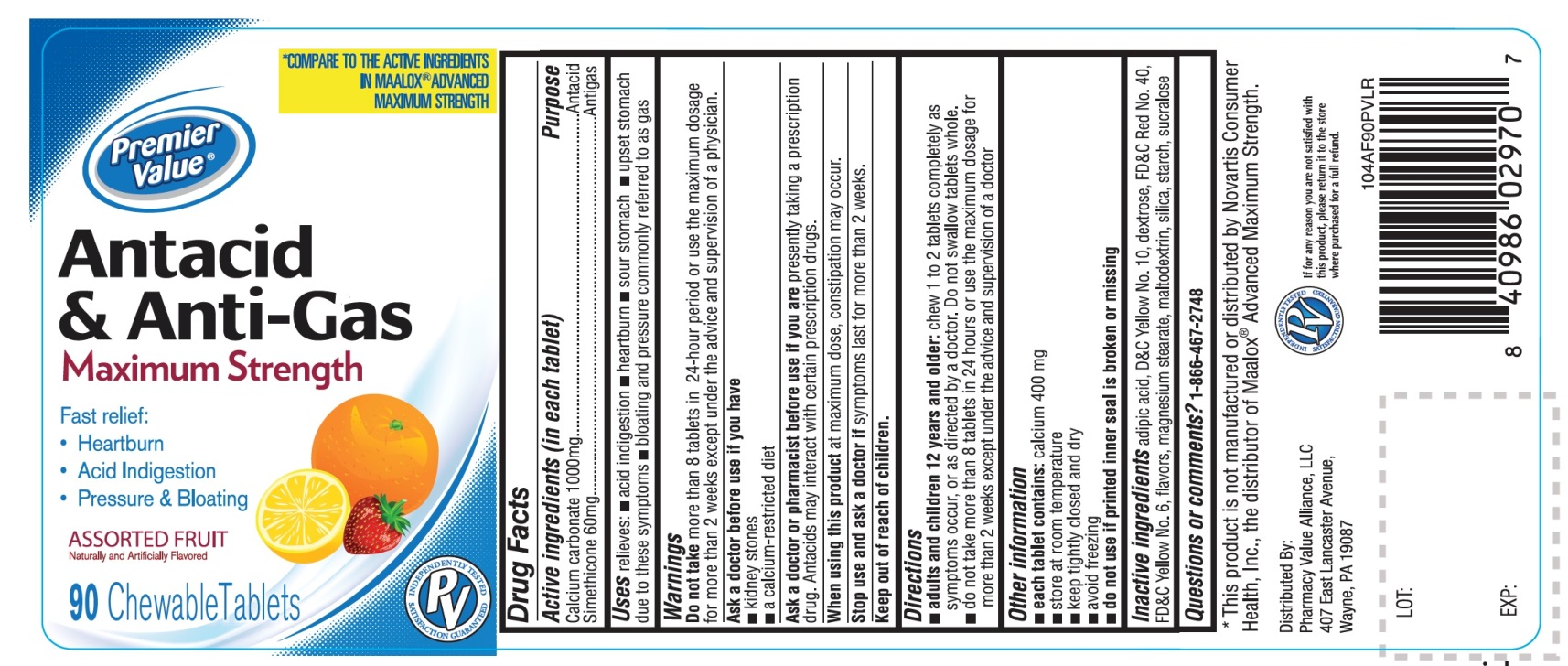 DRUG LABEL: Premier Value Maximum Strength
NDC: 68016-249 | Form: TABLET, CHEWABLE
Manufacturer: PHARMACY VALUE ALLIANCE, LLC
Category: otc | Type: HUMAN OTC DRUG LABEL
Date: 20241025

ACTIVE INGREDIENTS: CALCIUM CARBONATE 1000 mg/1 1; DIMETHICONE, UNSPECIFIED 60 mg/1 1
INACTIVE INGREDIENTS: ADIPIC ACID; D&C YELLOW NO. 10; DEXTROSE, UNSPECIFIED FORM; FD&C RED NO. 40; FD&C YELLOW NO. 6; MAGNESIUM STEARATE; MALTODEXTRIN; SILICON DIOXIDE; STARCH, CORN; SUCRALOSE

Premier Value® Maximum Strength Antacid & Anti-Gas

Active ingredients (in each tablet)

Calcium carbonate 1000 mg

Simethicone 60 mg

Purpose

Antacid

Antigas

Uses

relieves:

- acid indigestion
- heartburn
- sour stomach
- upset stomach due to these symptoms
- bloating and pressure commonly referred to as gas

Warnings

Do not take more than 8 tablets in 24 hours or use the maximum dosage for more than 2 weeks except under the advice and supervision of a doctor.

Ask a doctor before use if you have

- kidney stones
- a calcium-restricted diet

Ask a doctor or pharmacist before use if you are

presently taking a prescription drug. Antacids may interact with certain prescription drugs.

When using this product

at maximum dose, constipation may occur.

Stop use and ask a doctor if

symptoms persist for more than 2 weeks.

Directions

- adults and children 12 years and older: chew 1 to 2 tablets completely as symptoms occur or as directed by a doctor. Do not swallow tablets whole.
- do not take more than 8 tablets in 24 hours or use the maximum dosage for more than 2 weeks except under the advice and supervision of a doctor.

Other information

- each tablet contains: calcium 400 mg
- store at room temperature
- keep tightly closed and dry
- avoid freezing
- do not use if printed inner seal is broken or missing

Inactive ingredients

adipic acid, D&C Yellow No. 10, dextrose, FD&C Red No. 40, FD&C Yellow No. 6, flavors, magnesium stearate, maltodextrin, silica, starch, sucralose.

Questions or comments?

1-866-467-2748

Package/Label Principal Display Panel

Premier Value®

*COMPARE TO THE ACTIVE INGREDIENTS IN MAALOX® ADVANCED MAXIMUM STRENGTH

NDC: 68016-249-00

Antacid & Anti-Gas

MAXIMUM STRENGTH

Fast relief of:

- Heartburn
- Acid indigestion
- Pressure & bloating
Assorted Fruit
Naturally Artificially Flavored

90 Chewable Tablets

INDEPENDENTLY TESTED PV SATISFACTION GURANTEED

Distributed by:

Pharmacy Value Alliance, LLC

407 East Lancaster Avenue,

Wayne, PA 19087

If for any reason you are not satisfied with this product, please return it to the store where purchased for a full refund.

*This product is not manufactured or distributed by Novartis Consumer Health, Inc., the distributor of Maalox® Advanced Maximum Strength.